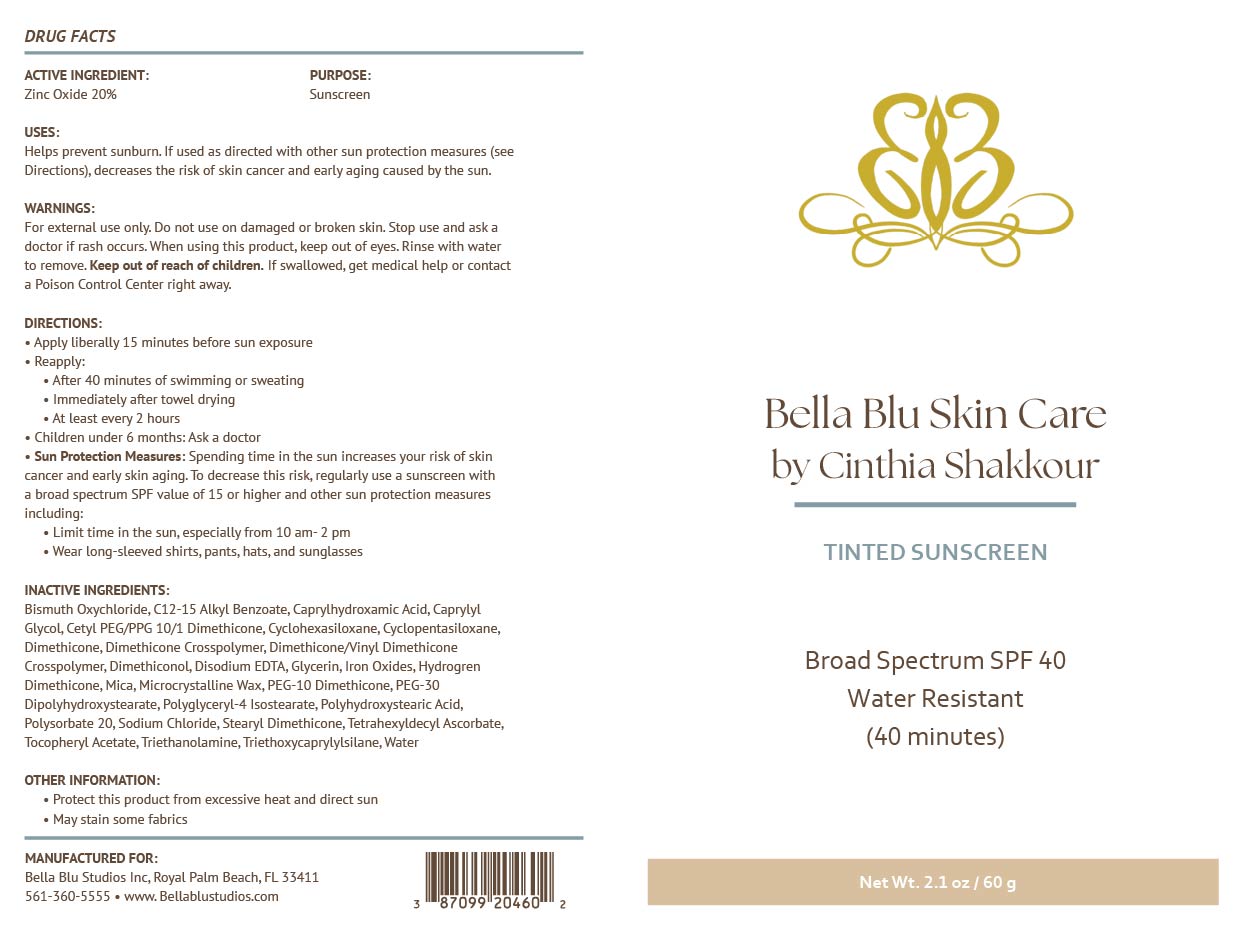 DRUG LABEL: Bella Blue Skin Care Tinted Sunscreen
NDC: 87099-204 | Form: CREAM
Manufacturer: BELLA BLU STUDIOS INC
Category: otc | Type: HUMAN OTC DRUG LABEL
Date: 20251217

ACTIVE INGREDIENTS: ZINC OXIDE 200 mg/1 g
INACTIVE INGREDIENTS: CAPRYLYL GLYCOL; CYCLOPENTASILOXANE; HYDROGEN DIMETHICONE (20 CST); PEG-30 DIPOLYHYDROXYSTEARATE; SODIUM CHLORIDE; POLYSORBATE 20; BISMUTH OXYCHLORIDE; CI 77491; C12-15 ALKYL BENZOATE; CI 77499; CI 77492; POLYHYDROXYSTEARIC ACID (2300 MW); CAPRYLHYDROXAMIC ACID; EDETATE DISODIUM ANHYDROUS; POLYGLYCERYL-4 ISOSTEARATE; TRIETHOXYCAPRYLYLSILANE; DIMETHICONE; MICA; CYCLOHEXASILOXANE; DIMETHICONE CROSSPOLYMER; MICROCRYSTALLINE WAX; PEG-10 DIMETHICONE (600 CST); TRIETHANOLAMINE; STEARYL DIMETHICONE (400 MPA.S AT 50C); WATER; CETYL PEG/PPG-10/1 DIMETHICONE (HLB 4); ALPHA-TOCOPHEROL ACETATE; DIMETHICONOL (2000 CST); DIMETHICONE/VINYL DIMETHICONE CROSSPOLYMER (SOFT PARTICLE); GLYCERIN; TETRAHEXYLDECYL ASCORBATE

Active Ingredients:

Zinc Oxide 20%

Purpose:

Sunscreen

Uses:

Helps Prevent Sunburn. If used as directed with other sun protection measures (see “Directions”), decreases the risk of skin cancer and early skin aging caused by the sun.

Warnings:

For external use only. Do not use on broken or damaged skin. Stop use and ask a doctor if rash occurs. When using this product, keep out of eyes. Rinse with water to remove. Keep out of reach of children. If swallowed, get medical help or contact a poison control center right away.

Warnings:

Keep out of reach of children

Directions:

Apply liberally 15 minutes before sun exposure. Use a water-resistant product if swimming or sweating. Reapply at least every 2 hours. Children under 6 months: Ask a doctor. Sun Protection Measures: Spending time in the sun increases your risk of skin cancer and early skin aging. To decrease this risk, regularly use a sunscreen with a Broad-Spectrum SPF value of 15 or higher and other sun protection measures including: Limit time in the sun, especially from 10 a.m. - 2 p.m. Wear long-sleeved shirts, pants, hats and sunglasses.

Inactive Ingredients:

Bismuth Oxychloride, C12-15 Alkyl Benzoate, Caprylhydroxamic Acid, Caprylyl Glycol, Cetyl PEG/PPG-10/1 Dimethicone, Cyclohexasiloxane, Cyclopentasiloxane, Dimethicone, Dimethicone Crosspolymer, Dimethicone/Vinyl Dimethicone Crosspolymer, Dimethiconol, Disodium EDTA, Glycerin, Hydrogen Dimethicone, Iron Oxides, Mica, Microcrystalline Wax, PEG-10 Dimethicone, PEG-30 Dipolyhydroxystearate, Polyglyceryl-4 Isostearate, Polyhydroxystearic Acid, Polysorbate 20, Sodium Chloride, Stearyl Dimethicone, Tetrahexyldecyl Ascorbate, Tocopheryl Acetate, Triethanolamine, Triethoxycaprylylsilane, Water

Other Information:

- Protect this product from excessive heat and direct sun
- May stain some fabrics